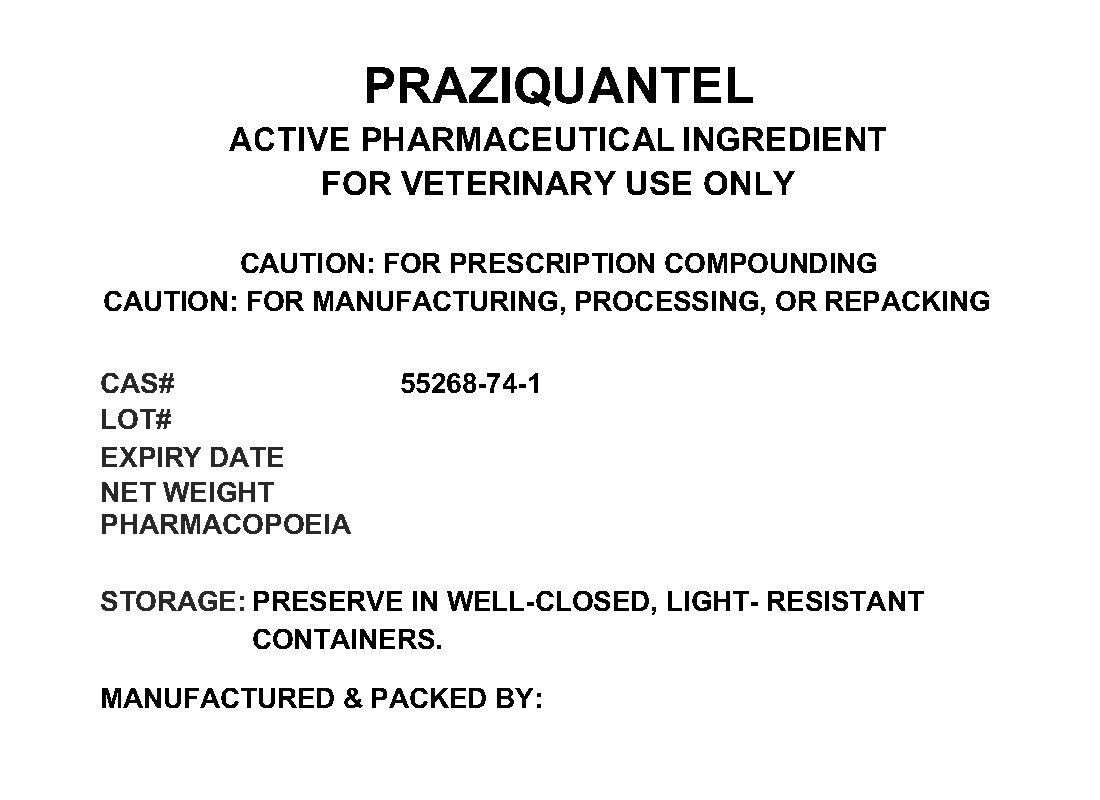 DRUG LABEL: PRAZIQUANTEL
NDC: 72969-118 | Form: POWDER
Manufacturer: PROFESSIONAL GROUP OF PHARMACISTS NEW YORK LLC
Category: other | Type: BULK INGREDIENT
Date: 20211221

ACTIVE INGREDIENTS: PRAZIQUANTEL 1 g/1 g

PRAZIQUANTEL

PACKAGE LABEL

praziquantellabel.jpg